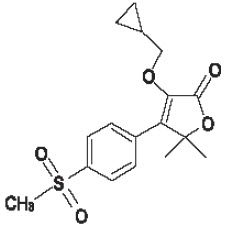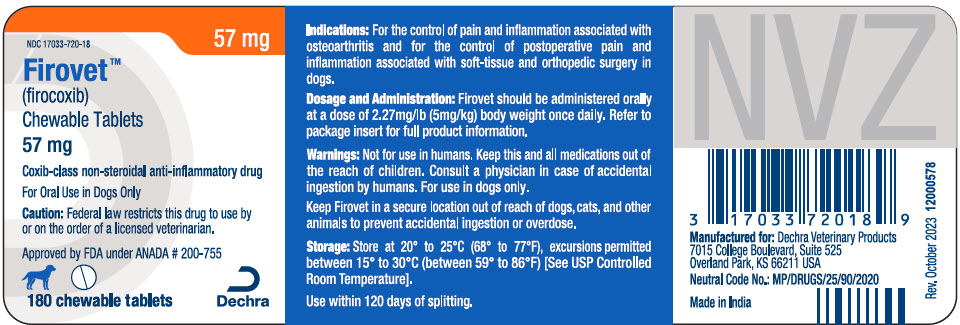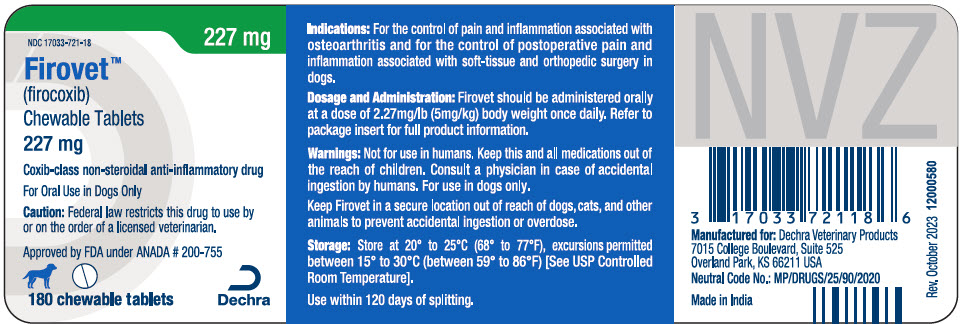 DRUG LABEL: Firovet
NDC: 17033-720 | Form: TABLET, CHEWABLE
Manufacturer: Dechra Vet Products, LLC
Category: animal | Type: PRESCRIPTION ANIMAL DRUG LABEL
Date: 20260212

ACTIVE INGREDIENTS: Firocoxib 57 mg/1 1

Firovet™
(firocoxib) Chewable Tablets

For oral use in dogs only.

Caution: Federal law restricts this drug to use by or on the order of a licensed veterinarian.

DESCRIPTION

Description: Firovet (lirocoxib) belongs to the coxib class of non-narcotic, non-steroidal anti-inflammatory drugs. Firocoxib is a white crystalline compound described chemically as 3-(cyclopropylmethoxy)-4-(4-(methylsulfonyl)phenyl)-5,5-dimethylfuranone. The empirical formula is C17H20O5S, and the molecular weight is 336.4. The structural formula is shown below:

PHARMACOKINETICS

Pharmacokinetics: The absolute bioavailability of Firovet (firocoxib) is approximately 38% when administered as a 5 mg/kg oral dose to fasted adult dogs. Firocoxib is rapidly cleared from the blood via hepatic metabolism and fecal excretion (CLsystemic=~0.4 L/hr/kg). Despite a high level of plasma protein binding (96%), firocoxib exhibits a large volume of distribution (Vdλ of total drug =~4.6 L/kg) and a terminal elimination half life of 7.8 hours (%CV = 30%). The oral drug absorption process is highly variable among subjects. Co-administration of Firovet with food delays drug absorption (Tmax from 1 to 5 hours) and decreases peak concentrations (Cmax from 1.3 to 0.9 mcg/ml). However, food does not affect the overall oral bioavailability at the recommended dose.

INDICATIONS AND USAGE

Indications: Firovet (firocoxib) chewable tablets are indicated for the control of pain and inflammation associated with osteoarthritits and for the control of postoperative pain and inflammation associated with soft-tissue and orthopedic surgery in dogs.

Dosage and Administration: Always provide the Client Information Sheet with prescription. Carefully consider the potential benefits and risks of Firovet and other treatment options before deciding to use Firovet. Use the lowest effective dose for the shortest duration consistent with individual response. The recommended dosage of Firovet (firocoxib) for oral administration in dogs is 2.27 mg/lb (5.0 mg/kg) body weight once daily as needed for osteoarthritis and for 3 days as needed for postoperative pain and inflammation associated with soft-tissue and orthopedic surgery. The dogs can be treated with Firovet approximately two hours prior to surgery. The tablets are scored and dosage should be calculated in half tablet increments. Firovet chewable tablets can be administered with or without food.

CONTRAINDICATIONS

Contraindications: Dogs with known hypersensitivity to firocoxib should not receive Firovet.

WARNINGS

Warnings: Not for use in humans. Keep this and all medications out of the reach of children. Consult a physician in case of accidental ingestion by humans.

For oral use in dogs only. Use of this product at doses above the recommended 2.27 mg/lb (5.0 mg/kg) in puppies less than seven months of age has been associated with serious adverse reactions, including death (see Animal Safety). Due to tablet sizes and scoring, dogs weighing less than 12.5 lb (5.7 kg) cannot be accurately dosed.

All dogs should undergo a thorough history and physical examination before the initiation of NSAID therapy. Appropriate laboratory testing to establish hematological and serum baseline data is recommended prior to and periodically during adminstration of any NSAID.

Owners should be advised to observe for signs of potential drug toxicity (see Adverse Reactions and Animal Safety) and be given a Client Information Sheet about Firovet chewable tablets.

To report suspected adverse drug events, for technical assistance or to obtain a copy of the Safety Data Sheet, contact Dechra at 1-866-933-2472. For additional information about adverse drug experience reporting for animal drugs, contact FDAat 1-888-FDA-VETS or http://www.fda.gov/reportanimalae

Keep Firovet in a secure location out of reach of dogs, cats, and other animals to prevent accidental ingestion or overdose.

PRECAUTIONS

Precautions: This product cannot be accurately dosed in dogs less than 12.5 pounds in bodyweight.

Consider appropriate washout times when switching from one NSAID to another or when switching from corticosteroid use to NSAID use.

As a class, cyclooxygenase inhibitory NSAIDs may be associated with renal, gastrointestinal and hepatic toxicity. Sensitivity to drug-associated adverse events varies with the individual patient. Dogs that have experienced adverse reactions from one NSAID may experience adverse reactions from another NSAID. Patients at greatest risk for adverse events are those that are dehydrated, on concomitant diuretic therapy, or those with existing renal, cardiovascular, and/or hepatic dysfunction. Concurrent administration of potentially nephrotoxic drugs should be carefully approached and monitored. NSAIDs may inhibit the prostaglandins that maintain normal homeostatic function. Such anti-prostaglandin effects may result in clinically significant disease in patients with underlying or pre-existing disease that has not been previously diagnosed. Since NSAIDS possess the potential to produce gastrointestinal ulceration and/or gastrointestinal perforation, concomitant use of Firovet chewable tablets with other anti-inflammatory drugs, such as NSAIDs or corticosteroids, should be avoided. The concomitant use of protein bound drugs with Firovet chewable tablets has not been studied in dogs. Commonly used protein-bound drugs include cardiac, anticonvulsant, and behavioral medications. The influence of concomitant drugs thal may inhibit the metabolism of Firovet chewable tablets has not been evaluated.

Drug compatibility should be monitored in patients requiring adjunctive therapy.

If additional pain medication is needed after the daily dose of Firovet, a non-NSAID class of analgesic may be necessary.

Appropriate monitoring procedures should be employed during all surgical procedures. Anesthetic drugs may affect renal perfusion, approach concomitant use of anesthetics and NSAIDs cautiously. The use of parenteral fluids during surgery should be considered to decrease potential renal complications when using NSAIDs perioperatively.

The safe use of Firovet chewable tablets in pregnant, lactating or breeding dogs has not been evaluated.

Adverse Reactions:

Osteoarthritis: In controlled field studies, 128 dogs (ages 11 months to 15 years) were evaluated for safety when given firocoxib chewable tablets at a dose of 2.27 mg/lb (5.0 mg/kg) orally once daily for 30 days. The following adverse reactions were observed. Dogs may have experienced more than one of the observed adverse reactions during the study.

Adverse Reactions Seen in U.S. Field Studies
Adverse Reactions | Firocoxib n=128 | Active Control n=121
Vomiting | 5 | 8
Diarrhea | 1 | 10
Decreased Appetite or Anorexia | 3 | 3
Lethargy | 1 | 3
Pain | 2 | 1
Somnolence | 1 | 1
Hyperactivity | 1 | 0

Firocoxib chewable tablets were safely used during field studies concomitantly with other therapies, including vaccines, anthelmintics, and antibiotics.

Soft-tissue Surgery: In controlled field studies eveluating soft-tissue postoperative pain and inflammation, 258 dogs (ages 10.5 weeks to 16 years) were eveluated for safety when given firocoxib chewable tablets at a dose of 2.27 mg/lb (5.0 mg/kg) orally approximately 2 hours prior to surgery and once daily thereafter for up to two days. The following adverse reactions were observed. Dogs may have experienced more than one of the observed reactions during the study.

Adverse Reactions Seen in the Soft-tissue Surgery Postoperative Pain Field Studies
Adverse Reactions | Firocoxib Group n=127 | Control Group [Sham-dosed (pilled)] n=131
Vomiting | 5 | 6
Diarrhea | 1 | 1
Bruising at Surgery Site | 1 | 1
Respiratory Arrest | 1 | 0
SQ Crepitus in Rear Leg and Flank | 1 | 0
Swollen Paw | 1 | 0

Orthopedic Surgery: In a controlled field study evaluating orthopedic postoperative pain and inflammation, 226 dogs of various breeds, ranging in age from 1 to 11.9 years in the firocoxib-treated groups and 0.7 to 17 years in the control group were evaluated for safety. Of the 226 dogs, 118 were given firocoxib chewable tablets at a dose of 2.27 mg/lb (5.0 mg/kg) orally approximately 2 hours prior to surgery and once daily thereafter for a total of three days. The following adverse reactions were observed. Dogs may have experienced more than one of the observed reactions during the study.

Adverse Reactions Seen in the Orthopedic Surgery Postoperative Pain Field Study
Adverse Reactions | Firocoxib Group n=118 | Control Group [Sham-dosed (pilled).] n=108
Vomiting | 1 | 0
Diarrhea | 2 [One dog had hemorrhagic gastroenteritis.] | 1
Bruising at Surgery Site | 2 | 3
Inappetence/Decreased Appetite | 1 | 2
Pyrexia | 0 | 1
Incision Swelling, Redness | 9 | 5
Oozing Incision | 2 | 0
A case may be represented in more than one category.

Post-Approval Experience (Rev. 2009): The following adverse reactions are based on post-approval adverse drug event reporting. The categories are listed in decreasing order of frequency by body system:

Gastrointestinal: vomiting, anorexia, diarrhea, melena, gastrointestinal perforation, hematemesis, hematachezia, weightloss, gastrointestinal ulceration, peritonitis, abdominal pain, hypersalivation, nausea

Urinary: elevated BUN, elevated creatinine, polydypsia, polyuria, hematuria, urinary incontinence, proteinuria, kidnay failure, azotemia, urinary tract infection

Neurological/Behavioral/Special Sense: depression/lethargy, ataxia, seizures, nervousness, confusion, weakness, hyperactivity, tremor, paresis, head tilt, nystagmus, mydriasis, aggression, uveitis.

Hepatic: elevated ALP, elevated ALT, elevated bilirubin, decreased albumin, elevated AST, icterus, decreased or increased total protein and globulin, pancreatitis, ascites, liver failure, decreased BUN

Hematological: anemia, neutrophilia, thrombocytopenia, neutropenia

Cardiovascular/Respiratory: tachypnea, dyspnea, tachycardia

Dermatologic/Immunologic: pruritis, fever, alopecia, moist dermatitis, autoimmune hemolytic anemia, facial/muzzle edema, urticaria

In some cases, death has been reported as an outcome of the adverse events listed above.

Contact Information: To report suspected adverse drug events, for technical assistance or to obtain a copy of the Safety Data Sheet, contact Dechra at 1-866-933-2472. For additional information about adverse drug experience reporting for animal drugs, contact FDA at 1-888-FDA-VETS or http://www.fda.gov/reportanimalae

INFORMATION FOR OWNERS/CAREGIVERS

Information For Dog Owners: Firovet, like other drugs of its class, is not free from adverse reactions. Owners should be advised of the potential for adverse reactions and be informed of the clinical signs associated with drug intolerance.

Adverse reactions may include vomiting, diarrhea, decreased appetite, dark or tarry stools, increased water consumption, increased urination, pale gums due to anemia, yellowing of gums, skin or white of the eye due to jaundice, lethargy, incoordination, seizure, or behavioral changes.

Serious adverse reactions associated with this drug class can occur without warning and in rare situations result in death (see Adverse Reactions). Owners should be advised to discontinue Firovet therapy and contact their veterinarian immediately if signs of intolerance are observed. The vast majority of patients with drug related adverse reactions have recovered when the signs are recognized, the drug is withdrawn, and veterinary care, if appropriate, is initiated. Owners should be advised of the importance of periodic follow up for all dogs during administration of any NSAID.

CLINICAL PHARMACOLOGY

Clinical Pharmacology: Mode of action: Firovet (firocoxib) is a cyclooxygenase-inhibiting (coxib) class, non-narcotic, non-steroidal anti-inflammatory drug (NSAID) with anti-inflammatory and analgesic properties. There are two main cyclooxygenase enzymes, COX-1 and COX-2, and a newly discovered third enzyme, COX-3, which has yet to be fully characterized.^1 Cyclooxygenase-1 (COX-1) is the enzyme responsible for facilitating constitutive physiologic processes, e.g., platelet aggregation, gastric mucosal protection, and renal perfusion.^2 It also is constitutively expressed in the brain, spinal cord, and reproductive tract.^3 Cyclooxygenase-2 (COX-2) is responsible for the synthesis of inflammatory mediators, but it is also constitutively expressed in the brain, spinal cord and kidneys.^4,5,6 Cyclooxygenase-3 (COX-3) is also constitutively expressed in the canine and human brain and also the human heart.^7 Results from in vitro studies showed firocoxib to be highly selective for the COX-2 enzyme when canine blood was exposed to drug concentrations comparable to those observed following a once daily 5 mg/kg oral dose in dogs.^8 However, the clinical significance of these findings has not been established.

Effectiveness: Two hundred and forty-nine dogs of various breeds, ranging in age from 11 months to 20 years, and weighing 13 to 175 lbs, were randomly administered firocoxib or an active control drug in two field studies. Dogs were assessed for lameness, pain on manipulation, range of motion, joint swelling, and overall improvement in a non-inferiority evaluation of firocoxib compared with the active control. At the study's end, 87% of the owners rated firocoxib-treated dogs as improved. Eighty-eight percent of dogs treated with firocoxib were also judged improved by the veterinarians. Dogs treated with firocoxib showed a level of improvement in veterinarian-assessed lameness, pain on palpation, range of motion, and owner-assessed improvement that was comparable to the active control. The level of improvement in firocoxib-treated dogs in limb weight bearing on the force plate gait analysis assessment was comparable to the active control.

In a separate field study, two hundred fifty-eight client-owned dogs of various breeds, ranging in age from 10.5 weeks to 16 years and weighing from 7 to 168 lbs, were randomly administered firocoxib or a control (sham-dosed-pilled) for the control of postoperative pain and inflammation associated with soft-tissue surgical procedures such as abdominal surgery (e.g. ovariohysterectomy, abdominal cryptorchidectomy, splenectomy, cystotomy) or major external surgeries (e.g. mastectomy, skin tumor removal ≥8 cm). The study demonstrated that firocoxib-treated dogs had significantly lower need for rescue medication than the control (sham-dosed-pilled) in controlling postoperative pain and inflammation associated with soft-surgery.

A multi-center field study with 226 client-owned dogs of various breeds, and ranging in age from 1 to 11.9 years in the firocoxib-treated groups and 0.7 to 17 years in the control group was conducted. Dogs were randomly assigned to either the firocoxib or the control (sham-dosed-pilled) group for the control of postoperative pain and inflammation associated with orthopedic surgery. Surgery to repair a ruptured cruciate ligament included the following stabilization procedures: fabellar suture and/or imbrication, fibular head transposition, tibial plateau leveling osteotomy (TPLO), and 'over the top' technique. The study (n = 220 for effectiveness) demonstrated that firocoxib-treated dogs had significantly lower need for rescue medication than the control (sham-dosed-pilled) in controlling postoperative pain and inflammation associated with orthopedic surgery.

ANIMAL PHARMACOLOGY AND OR TOXICOLOGY

Animal Safety: In a target animal safety study, firocoxib was administered orally to healthy adult Beagle dogs (eight dogs per group) at 5, 15, and 25 mg/kg (1, 3, and 5 times the recommended total daily dose) for 180 days. At the indicated dose of 5 mg/kg, there were no treatment related adverse events. Decreased appetite, vomiting, and diarrhea were seen in dogs in all dose groups, including unmedicated controls, although vomiting and diarrhea were seen more often in dogs in the 5× dose group. One dog in the 3× dose group was diagnosed with juvenile polyarteritis of unknown etiology after exhibiting recurrent episodes of vomiting and diarrhea, lethargy, pain, anorexia, ataxia, proprioceptive deficits, decreased albumin levels, decreased and then elevated platelet counts, increased bleeding times, and elevated liver enzymes. On histopathologic examination, a mild ileal ulcer was found in one 5× dog. This dog also had a decreased serum albumin which returned to normal by study completion. One control and three 5× dogs had focal areas of inflammation in the pylorus or small intestine. Vacuolization without inflammatory cell infiltrates was noted in the thalamic region of the brain in three control, one 3×, and three 5× dogs. Mean ALP was within the normal range for all groups but was greater in the 3× and 5× dose groups than in the control group. Transient decreases in serum albumin were seen in multiple animals in the 3× and 5× dose groups, and in one control animal.

In a separate safety study, firocoxib was administered orally to healthy juvenile (10-13 weeks of age) Beagle dogs at 5, 15, and 25 mg/kg (1, 3, and 5 times the recommended total daily dose) for 180 days. At the indicated (1×) dose of 5 mg/kg, on histopathologic examination, three out of six dogs had minimal periportal hepatic fatty change. On histopathologic examination, one control, one 1×, and two 5× dogs had diffuse slight hepatic fatty change. These animals showed no clinical signs and had no liver enzyme elevations. In the 3× dose group, one dog was euthanized because of poor clinical condition (Day 63). This dog also had a mildly decreased serum albumin. At study completion, out of five surviving and clinically normal 3× dogs, three had minimal periportal hepatic fatty change. Of twelve dogs in the 5× dose group, one died (Day 82) and three moribund dogs were euthanized (Days 38, 78, and 79) because of anorexia, poor weight gain, depression, and in one dog, vomiting. One of the euthanized dogs had ingested a rope toy. Two of these 5× dogs had mildly elevated liver enzymes. At necropsy all five of the dogs that died or were euthanized had moderate periportal or severe panzonal hepatic fatty change; two had duodenal ulceration; and two had pancreatic edema. Of two other clinically normal 5× dogs (out of four euthanized as comparators to the clinically affected dogs), one had slight and one had moderate periportal hepatic fatty change. Drug treatment was discontinued for four dogs in the 5× group. These dogs survived the remaining 14 weeks of the study. On average, the dogs in the 3× and 5× dose groups did not gain as much weight as control dogs. Rate of weight gain was measured (instead of weight loss) because these were young growing dogs. Thalamic vacuolation was seen in three of six dogs in the 3× dose group, five of twelve dogs in the 5× dose group, and to a lesser degree in two unmedicated controls. Diarrhea was seen in all dose groups, including unmedicated controls.

In a separate dose tolerance safety study involving a total of six dogs (two control dogs and four treated dogs), firocoxib was administered to four healthy adult Beagle dogs at 50 mg/kg (ten times the recommended daily dose) for twenty-two days. All dogs survived to the end of the study. Three of the four treated dogs developed small intestinal erosion or ulceration. Treated dogs that developed small intestinal erosion or ulceration had a higher incidence of vomiting, diarrhea, and decreased food consumption than control dogs. One of these dogs had severe duodenal ulceration, with hepatic fatty change and associated vomiting, diarrhea, anorexia, weight loss, ketonuria, and mild elevations in AST and ALT. All four treated dogs exhibited progressively decreasing serum albumin that, with the exception of one dog that developed hypoalbuminemia, remained within normal range. Mild weight loss also occurred in the treated group. One of the two control dogs and three of the four treated dogs exhibited transient increases in ALP that remained within normal range.

STORAGE AND HANDLING

Storage: Store at 20° to 25°C (68° to 77°F), excursions permitted between 15° to 30°C (between 59° to 86°F) [See USP Controlled Room Temperature].

To Request a Safety Data Sheet (SDS), call 1-866-933-2472.

HOW SUPPLIED

How Supplied: Firovet is available as round, brownish yellow to pale brown, half-scored tablets in two strengths, containing 57 mg or 227 mg firocoxib. Each tablet strength is supplied in 60 count and 180 count bottles.

NDC Number | Tablet Size | Package Description
17033-720-60 | 57 mg | 60 in Bottle pack
17033-720-18 | 57 mg | 180 in Bottle pack
17033-721-60 | 227 mg | 60 in Bottle pack
17033-721-18 | 227 mg | 180 in Bottle pack

REFERENCES

^1 Willoughby DA, Moore AR and Colville-Nash PR. COX-1, COX-2, and COX-3 and the future treatment of chronic inflammatory disease. Lancet 2000; 355: 646-648.
^2 Smith, et al., Pharmacological Analysis of Cyclo-oxygenase-1 in Inflammation. Proc. Natl. Acad. Sci. USA, Pharmacology 1998; 95: 13313-13318.
^3 Jones CJ and Budsberg SC, Physiologic characteristics and clinical importance of the cyclooxygenase isoforms in dogs and cats. JAVMA 2000; 217(5): 721-729.
^4 Zhang, et al., Inhibition of Cyclo-oxygenase-2 Rapidly Reverses Inflammatory Hyperalgesia and Prostaglandin E2 Production. JPET 1997; 283: 1069-1075.
^5 Jones and Budsberg, pp. 721-729.
^6 Zhang, et al., pp. 1069-1075.
^7 Chandrasekharan NV, Dai H, et al. COX-3, a cyclooxygenase-1 variant inhibited by acetaminophen and other analgesic/antipyretic drugs: Cloning, structure and expression. Proc. Natl. Acad. Sci. USA, 2002; 99(21): 13926-13931.
^8 Data on file with NADA# 141-230.

Manufactured for:
Dechra Veterinary Products
7015 College Boulevard, Suite 525
Overland Park, KS 66211 USA

Made in India

Neutral Code No. MP/DRUGS/25/90/2020

Rev. October 2023

Approved by FDA under ANADA # 200-755

Firovet is a trademark of Dechra Veterinary Products, LLC

Information for Dog Owners about Firovet™ (firocoxib) Chewable Tablets

Firovet chewable tablets are used for the control of pain and inflammation due to osteoarthritis or associated with soft-tissue and orthopedic surgery in your dog.

This summary contains important information about Firovet. You should read this information before you start giving your dog Firovet tablets and review it each time your prescription is refilled. This sheet is provided only as a summary and does not take the place of instructions from your veterinarian. Talk to your veterinarian if you do not understand any of this information or you want to know more about Firovet.

What is Firovet?

Firovet is a veterinary prescription non-steroidal anti-inflammatory drug (NSAID) used to control pain and inflammation due to osteoarthritis, or associated with soft tissue and orthopedic surgery in dogs.

Osteoarthritis is a painful condition ceused by "wear and tear" of cartilage and other parts of the joints that may result in the following changes or signs in your dog:

- Limping or lameness.
- Decreased activity or exercise (reluctance to stand, climb stairs, jump or run, or difficulty in performing these activities).
- Stiffness or decreased movement of joints.

Firovet is indicated for the control of postoperative pain and inflammation following soft-tissue and orthopedic surgeries (e.g. spays, cruciate ligament repair). Your veterinarian may administer Firovet before the procedure and recommend that the dog be treated for a few days after going home.

What kind of results can I expect when my dog is on Firovet for osteoarthritis?

While Firovet is not a cure for osteoarthritis, it can control the pain and inflammation and improve your dog's mobility.

- Response varies from dog to dog, but improvement cen be quite dramatic.
- In most dogs, improvement can be seen within days.
- If Firovet is discontinued or not given as directed, your dog's pain and inflammation may return.

What kind of results can I expect when my dog is on Firovet for the control of pain and inflammation following soft-tissue and orthopedic surgery?

- Firovet chewable tablets allow your dog to recover more comfortably by controlling pain and inflammation following soft-tissue and orthopedic surgery.
- Control of pain and inflammation may vary from dog to dog.
- If Firovet chewable tablets are not given according to your veterinarian's directions, your dog's pain may return.
- Consult your veterinarian if your dog appears to be uncomfortable.

Which dogs should not take Firovet?

Your dog should not be given Firovet if he/she:

- Has an allergic reaction to firocoxib, the active ingredient in Firovet.
- Has had an allergic reaction (such as hives, facial swelling, or red or itchy skin) to aspirin or other NSAIDs.
- Is presently taking aspirin, other NSAIDs, or corticosteroids.
- Is under 12.5 pounds in body weight.
- Has pre-existing kidney or liver disease.
- Has decreased appetite, vomiting or diarrhea.

Firovet should only be given to dogs.

People should not take Firovet. Keep Firovet and all medications out of the reach of children. Call your physician immediately if you accidentally take Firovet.

What to tell/ask your veterinarian before giving Firovet.

Talk to your veterinarian about:

- The signs of osteoarthritis you have observed in your dog, such as limping or stiffness.
- The importance of weight control in the management of osteoarthritis.
- What tests might be done before Firovet is prescribed.
- How often your dog may need to be examined by your veterinarian.
- The risks and benefits of using Firovet. Serious adverse reactions, including death, have been associated with Firovet administration at doses above the recommended dose in puppies less than seven months of age.

Tell your veterinarian if your dog is currently experiencing or has ever had the following medical problems:

- Any side effects from taking Firovet or other NSAIDs, such as aspirin.
- Any digestive upset (vomiting and/or diarrhea).
- Any kidney disease.
- Any liver disease.

Tell your veterinarian about:

- Any other medical problems or allergies that your dog has now, or has had in the past.
- All medicines that you are giving or plan to give to your dog, including those you can get without a prescription and any dietary supplements.

Tell your veterinarian if your dog:

- Is under 7 months of age.
- Is pregnant, nursing or if you plan to breed your dog.

How to give Firovet to your dog.

Firovet should be given according to your veterinarian's instructions. Do not change the way you give Firovet to your dog without first speaking with your veterinarian.

Your veterinarian will tell you what amount of Firovet is right for your dog and for how long it should be given. Firovet chewable tablets may be offered to the dog by hand, or you can place the tablet in your dog's mouth. Firovet may be given with or without food.

What are the possible side effects that may occur in my dog during Firovet therapy?

Firovet, like other NSAIDS, may cause some side effects. Serious side effects associated with NSAID therapy in dogs can occur with or without warning, and, in rare situations, result in death. The most common side effects associated with Firovet therapy involve the digestive tract (vomiting and decreased food consumption). Liver and kidney problems have also been reported with NSAIDs. Look for the following side effects that may indicate your dog is having a problem with Firovet:

- Decrease or increase in appetite.
- Vomiting.
- Change in bowel movements (such as diarrhea, or black, tarry or bloody stools).
- Change in behavior (such as decreased or increased activity level, incoordination, seizure, or aggression).
- Yellowing of gums, skin, or whites of the eyes (jaundice).
- Change in drinking habits (frequency or amount consumed).
- Change in urination habits (frequency, color, or smell).
- Change in skin (redness, scabs, or scratching).
- Unexpected weight loss.

It is important to stop the medication and contact your veterinarian immediately if you think your dog has a medical problem or side effect while taking Firovet tablets. If you have additional questions about possible side effects, talk with your veterinarian or call 1-866-933-2472.

Can Firovet be given with other medications?

Firovet should not be given with other NSAIDs (for example, aspirin, cerprofen, etodolac, deracoxib, meloxicam, or tepoxalin) or corticosteroids (for example, prednisone, cortisone, dexamethasone, or triamcinolone).

Tell your veterinarian about all medications that you have given your dog in the past, and any medications you are planning to give with Firovet tablets. This should include other medicines that you can get without a prescription or any dietary supplements. Your veterinarian may want to check that all of your dog's medicines can be given together.

What do I do in case my dog eats more than the prescribed amount of Firovet?

Consult your veterinarian immediately if your dog eats more than the prescribed amount of Firovet.

What else should I know about Firovet?

- This sheet provides a summary of information about Firovet tablets. If you have any questions or concerns about Firovet, osteoarthritis pain, or postoperative pain following soft-tissue and orthopedic surgery, talk with your veterinarian.
- As with all prescribed medicines, Firovet tablets should only be given to the dog for which they were prescribed. They should be given to your dog only for the condition for which they were prescribed, at the prescribed dose.
- It is important to periodically discuss your dog's response to Firovet tablets. Your veterinarian will determine if your dog is responding as expected and if your dog should continue receiving Firovet tablets.

Contact Information:

To report suspected adverse drug events, for technical assistance or to obtain a copy of Safety Data Sheet, contsct Dechra at 1-866-933-2472. For additional information about adverse drug experience reporting for animal drugs, contact FDA at 1-888-FDA-VETS or www.fda.gov/reportanimalae

Approved by FDA under ANADA # 200-755

Manufactured for:
Dechra Veterinary Products
7015 College Boulevard, Suite 525
Overland Park, KS 66211 USA

Made in India

Neutral Code No. MP/DRUGS/25/90/2020

Rev. October 2023

12000581

PRINCIPAL DISPLAY PANEL - 57 mg Tablet Bottle Label

NDC 17033-720-18

57 mg

Firovet™
(firocoxib)
Chewable Tablets
57 mg

Coxib-class non-steroidal anti-inflammatory drug

For Oral Use in Dogs Only

Caution: Federal law restricts this drug to use by
or on the order of a licensed veterinarian.

Approved by FDA under ANADA # 200-755

180 chewable tablets

Dechra

PRINCIPAL DISPLAY PANEL - 227 mg Tablet Bottle Label

NDC 17033-721-18

227 mg

Firovet™
(firocoxib)
Chewable Tablets
227 mg

Coxib-class non-steroidal anti-inflammatory drug

For Oral Use in Dogs Only

Caution: Federal law restricts this drug to use by
or on the order of a licensed veterinarian.

Approved by FDA under ANADA # 200-755

180 chewable tablets

Dechra